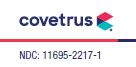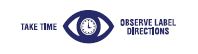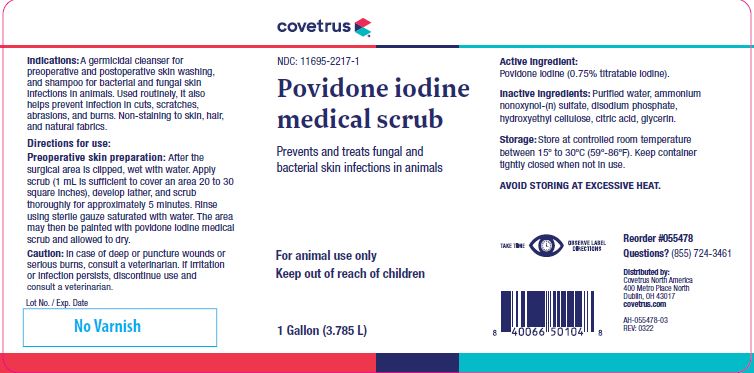 DRUG LABEL: Povidone iodine medical scrub
NDC: 11695-2217 | Form: LIQUID
Manufacturer: Butler Animal health Supply, LLC dba Covetrus North America
Category: animal | Type: OTC ANIMAL DRUG LABEL
Date: 20220926

ACTIVE INGREDIENTS: POVIDONE-IODINE 5.1 g/1 L

Povidone iodine medical scrub

VETERINARY INDICATIONS

Prevents and treats fungal and bacterial skin infections in animals

KEEP OUT OF REACH OF CHILDREN

For animal use only
Keep out of reach of children

HOW SUPPLIED

1 Gallon (3.785 L)

Indications:

A germicidal cleanser for preoperative and postoperative skin washing, and shampoo for bacterial and fungal skin infections in animals. Used routinely, it also helps prevent infection in cuts, scratches, abrasions, and burns. Non-staining to skin, hair, and natural fabrics.

Directions for use:

Preoperative skin preparation: After the surgical area is clipped, wet with water. Apply scrub (1 mL is sufficient to cover an area 20 to 30
square inches), develop lather, and scrub thoroughly for approximately 5 minutes. Rinse using sterile gauze saturated with water. The area may then be painted with povidone iodine medical scrub and allowed to dry.

Caution:

In case of deep or puncture wounds or serious burns, consult a veterinarian. If irritation or infection persists, discontinue use and consult a veterinarian.

Active ingredient:

Povidone iodine (0.75% titratable iodine).

Inactive ingredients:

Purified water, ammonium nonoxynol-(n) sulfate, disodium phosphate, hydroxyethyl cellulose, citric acid, glycerin.

Storage:

Store at controlled room temperature between 15º to 30ºC (59º-86ºF). Keep container tightly closed when not in use.
AVOID STORING AT EXCESSIVE HEAT.

INFORMATION FOR OWNERS/CAREGIVERS

Reorder #055478
Questions? (855) 724-3461
Distributed by:
Covetrus North America
400 Metro Place North
Dublin, OH 43017
covetrus.com

Manufactured by:
First Priority, Inc.
Elgin, IL 60123

AH-055478-03
REV: 0322